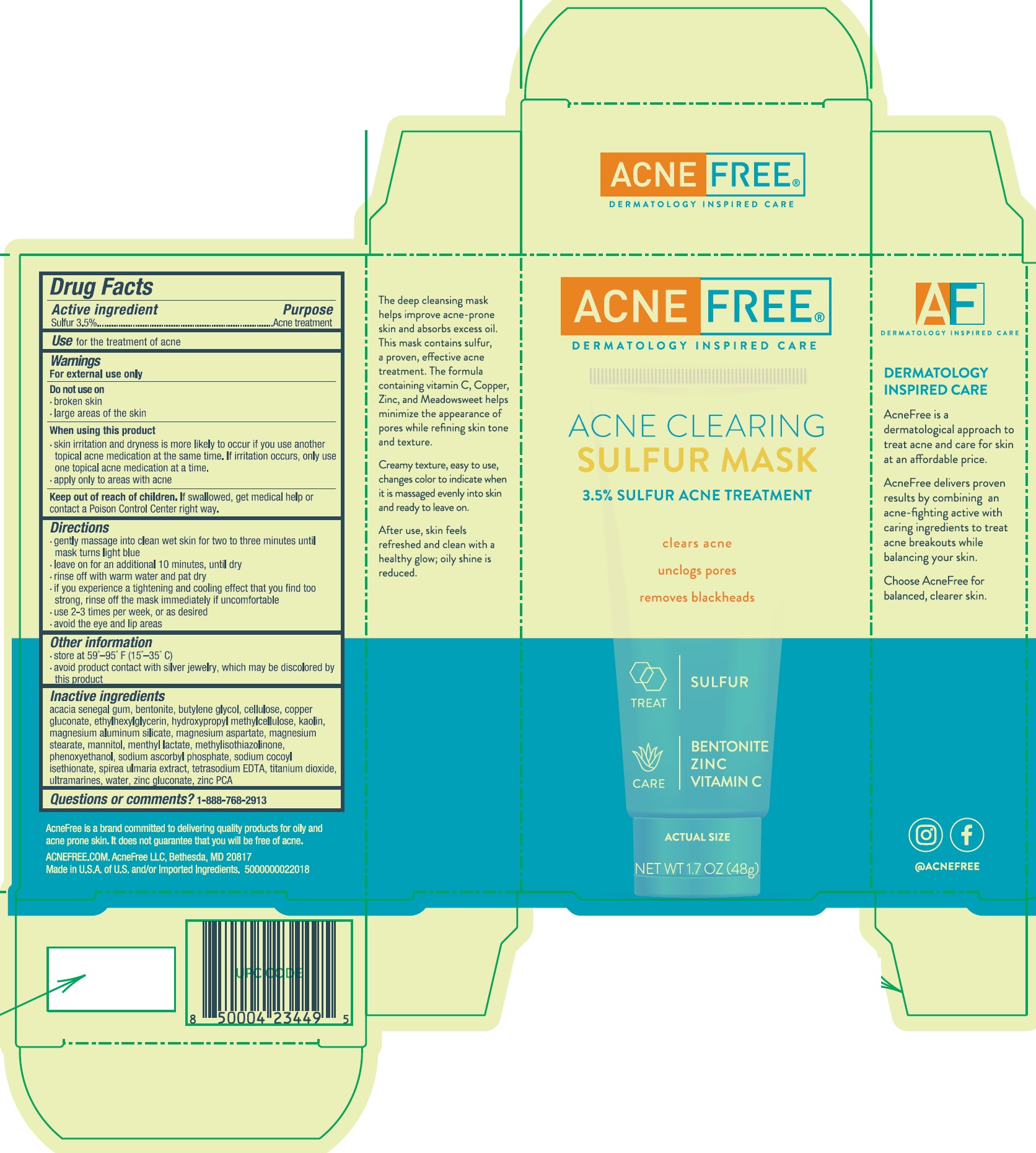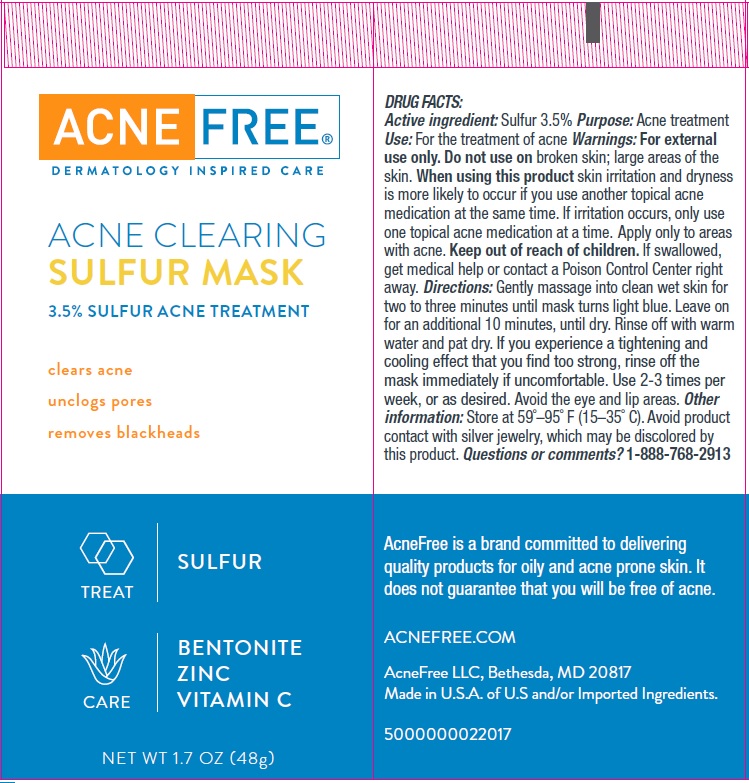 DRUG LABEL: Acne Clearing Sulfur Mask
NDC: 80861-001 | Form: CREAM
Manufacturer: AcneFree, LLC
Category: otc | Type: HUMAN OTC DRUG LABEL
Date: 20250724

ACTIVE INGREDIENTS: SULFUR 35 mg/1 g
INACTIVE INGREDIENTS: BUTYLENE GLYCOL; POWDERED CELLULOSE; COPPER GLUCONATE; ETHYLHEXYLGLYCERIN; HYPROMELLOSE, UNSPECIFIED; KAOLIN; MAGNESIUM ALUMINUM SILICATE; MAGNESIUM ASPARTATE; MAGNESIUM STEARATE; MANNITOL; METHYL LACTATE, (-)-; ACACIA; BENTONITE; METHYLISOTHIAZOLINONE; PHENOXYETHANOL; SODIUM ASCORBYL PHOSPHATE; SODIUM COCOYL ISETHIONATE; FILIPENDULA ULMARIA ROOT; EDETATE SODIUM; TITANIUM DIOXIDE; ULTRAMARINE BLUE; WATER; ZINC GLUCONATE; ZINC PIDOLATE

Acne Clearing Sulfur Mask

Active ingredient

Sulfur 3.5%

Purpose

Acne treatment

Use

for the treatment of acne

Warnings

For external use only

Do not use on

- broken skin
- large areas of the skin

When using this product

- skin irritation and dryness is more likely to occur if you use another topical acne medication at the same time. If irritation occurs, only use one topical acne medication at a time.
- apply only to areas with acne

Keep out of reach of children.

If swallowed, get medical help or contact a Poison Control Center right away.

Directions

- gently massage into clean wet skin for two to three minutes until mask turns light blue
- leave on for an additional 10 minutes, until dry
- rinse off with warm water and pat dry
- if you experience a tightening and cooling effect that you find too strong, rinse off the mask immediately if uncomfortable
- use 2-3 times per week, or as desired
- avoid the eye and lip areas

Other information

- store at 59°–95° F (15°–35° C)
- avoid product contact with silver jewelry, which may be discolored by this product

Inactive ingredients

acacia senegal gum, bentonite, butylene glycol, cellulose, copper gluconate, ethylhexylglycerin, hydroxypropyl methylcellulose, kaolin, magnesium aluminum silicate, magnesium aspartate, magnesium stearate, mannitol, methyl lactate, methylisothiazolinone, phenoxyethanol, sodium ascorbyl phosphate, sodium cocoyl isethionate, spirea ulmaria extract, tetrasodium EDTA, titanium dioxide, ultramarines, water, zinc gluconate, zinc PCA

Questions or comments?

1-888-768-2913